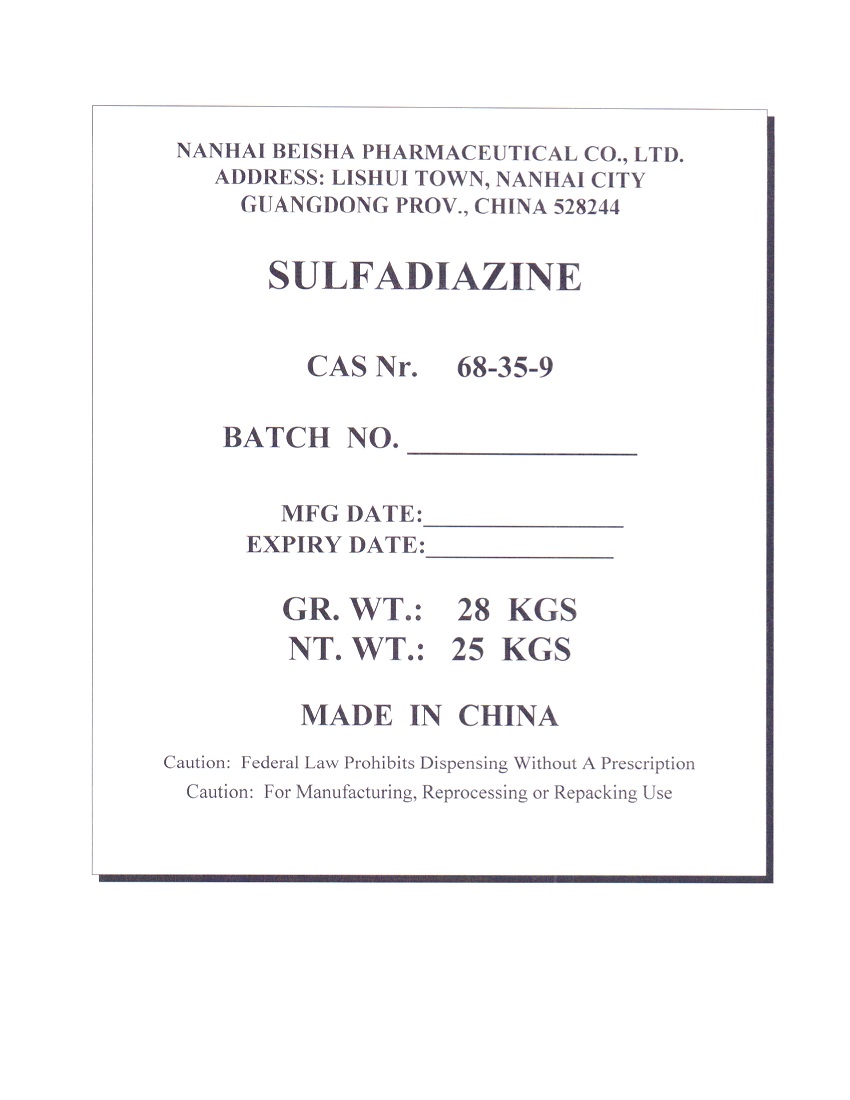 DRUG LABEL: SULFADIAZINE
NDC: 63422-703 | Form: POWDER
Manufacturer: NANHAI BEISHA PHARMACEUTICAL CO., LTD.
Category: other | Type: BULK INGREDIENT - ANIMAL DRUG
Date: 20250814

ACTIVE INGREDIENTS: SULFADIAZINE 25 kg/25 kg

PACKAGE LABEL

Add image transcription here...